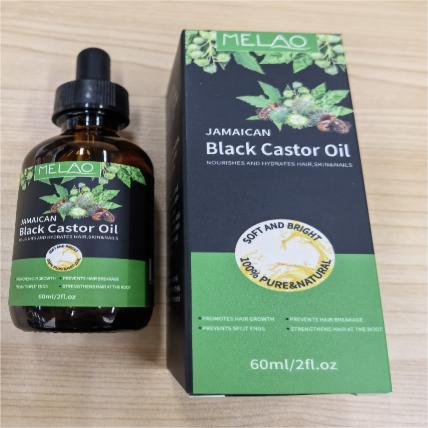 DRUG LABEL: MELAO JAMAICAN BLACK CASTOR
NDC: 83566-589 | Form: LIQUID
Manufacturer: Guangzhou Yilong Cosmetics Co., Ltd
Category: otc | Type: HUMAN OTC DRUG LABEL
Date: 20240820

ACTIVE INGREDIENTS: RICINUS COMMUNIS SEED 99.9 g/100 g
INACTIVE INGREDIENTS: ACAI OIL 0.1 g/100 g

MELAO JAMAICAN BLACK CASTOR

Active ingredients

Ricinus Communis (Castor) Seed Oil 100%

Purpose

Moisture

Uses

Step 1: Clean and thoroughly dry your skin.

Step 2: Rotate the bottle cap to open the product.

Step 3: Gently apply to the surface of the hair.

Warning

For external use only.

Stop use and ask a doctor if

rash occurs.

Do not use

on damaged or broken skin.

When using this product

keep out of eyes. Rinse withwater to remove.

keep out of eyes. Rinse withwater to remove.

If swallowed, get medical help or contact a Poison Control Center right away.

DOSAGE & ADMINISTRATION

Squeeze out an appropriate amount of product and spread evenly on skin.

inactive ingredient

oil 0.1%